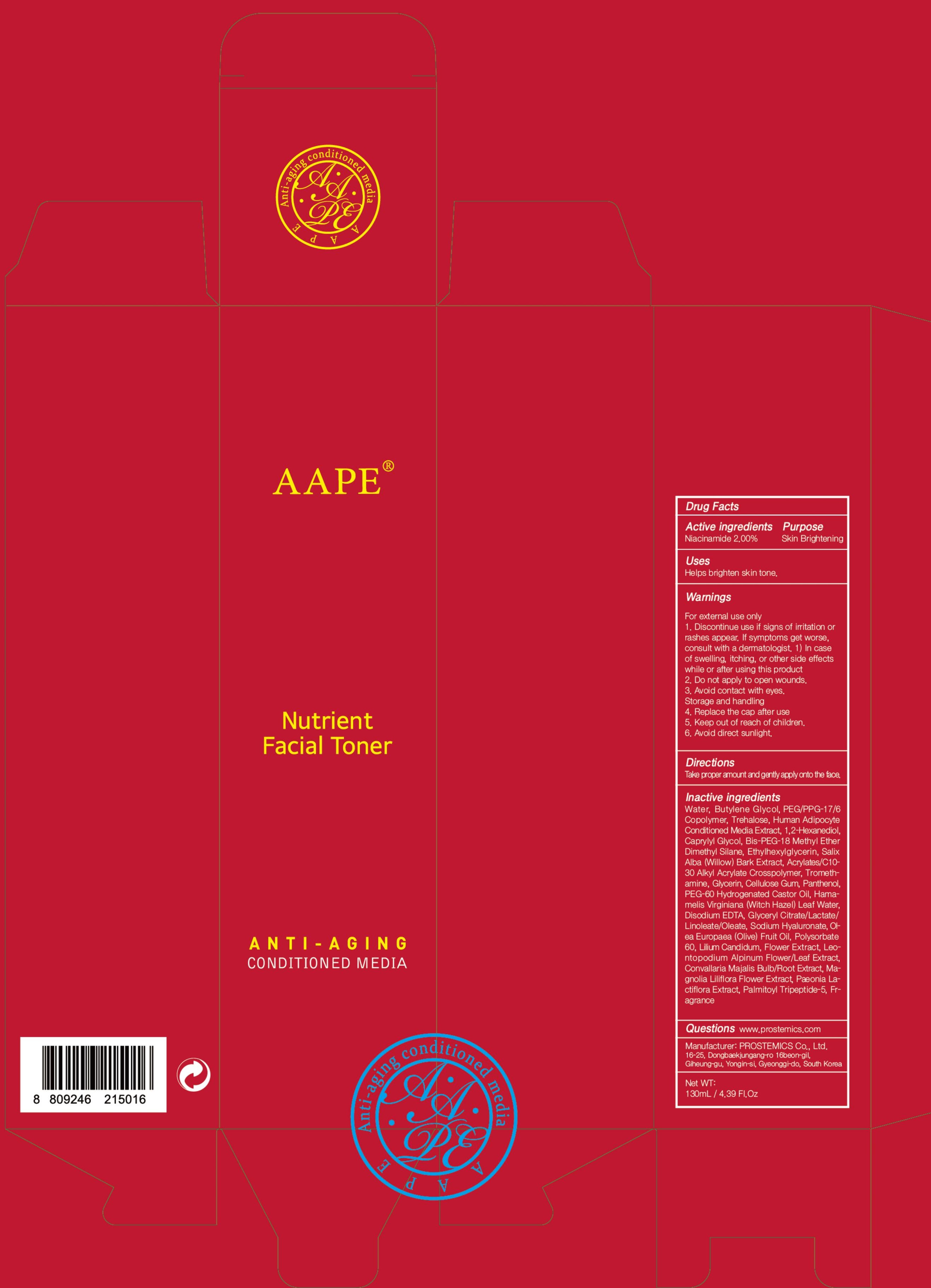 DRUG LABEL: AAPE Nutrient Facial Toner
NDC: 62041-200 | Form: LIQUID
Manufacturer: PROSTEMICS Co., Ltd.
Category: otc | Type: HUMAN OTC DRUG LABEL
Date: 20190822

ACTIVE INGREDIENTS: Niacinamide 2.60 g/130 mL
INACTIVE INGREDIENTS: Water; Butylene Glycol

ACTIVE INGREDIENT

Active ingredients: Niacinamide 2.00%

INACTIVE INGREDIENT

Inactive ingredients:
Water, Butylene Glycol, PEG/PPG-17/6 Copolymer, Trehalose, Human Adipocyte Conditioned Media Extract, 1,2-Hexanediol, Caprylyl Glycol, Bis-PEG-18 Methyl Ether Dimethyl Silane, Ethylhexylglycerin, Salix Alba (Willow) Bark Extract, Acrylates/C10-30 Alkyl Acrylate Crosspolymer, Tromethamine, Glycerin, Cellulose Gum, Panthenol, PEG-60 Hydrogenated Castor Oil, Hamamelis Virginiana (Witch Hazel) Leaf Water, Disodium EDTA, Glyceryl Citrate/Lactate/Linoleate/Oleate, Sodium Hyaluronate, Olea Europaea (Olive) Fruit Oil, Polysorbate 60, Lilium Candidum, Flower Extract, Leontopodium Alpinum Flower/Leaf Extract, Convallaria Majalis Bulb/Root Extract, Magnolia Liliflora Flower Extract, Paeonia Lactiflora Extract, Palmitoyl Tripeptide-5, Fragrance

PURPOSE

Purpose: Skin Brightening

WARNINGS

For external use only
1. Discontinue use if signs of irritation or rashes appear. If symptoms get worse, consult with a dermatologist. 1) In case of swelling, itching, or other side effects while or after using this product
2. Do not apply to open wounds.
3. Avoid contact with eyes.
Storage and handling
4. Replace the cap after use
5. Keep out of reach of children.
6. Avoid direct sunlight.

KEEP OUT OF REACH OF CHILDREN

Uses

Helps brighten skin tone.

Directions

Take proper amount and gently apply onto the face.